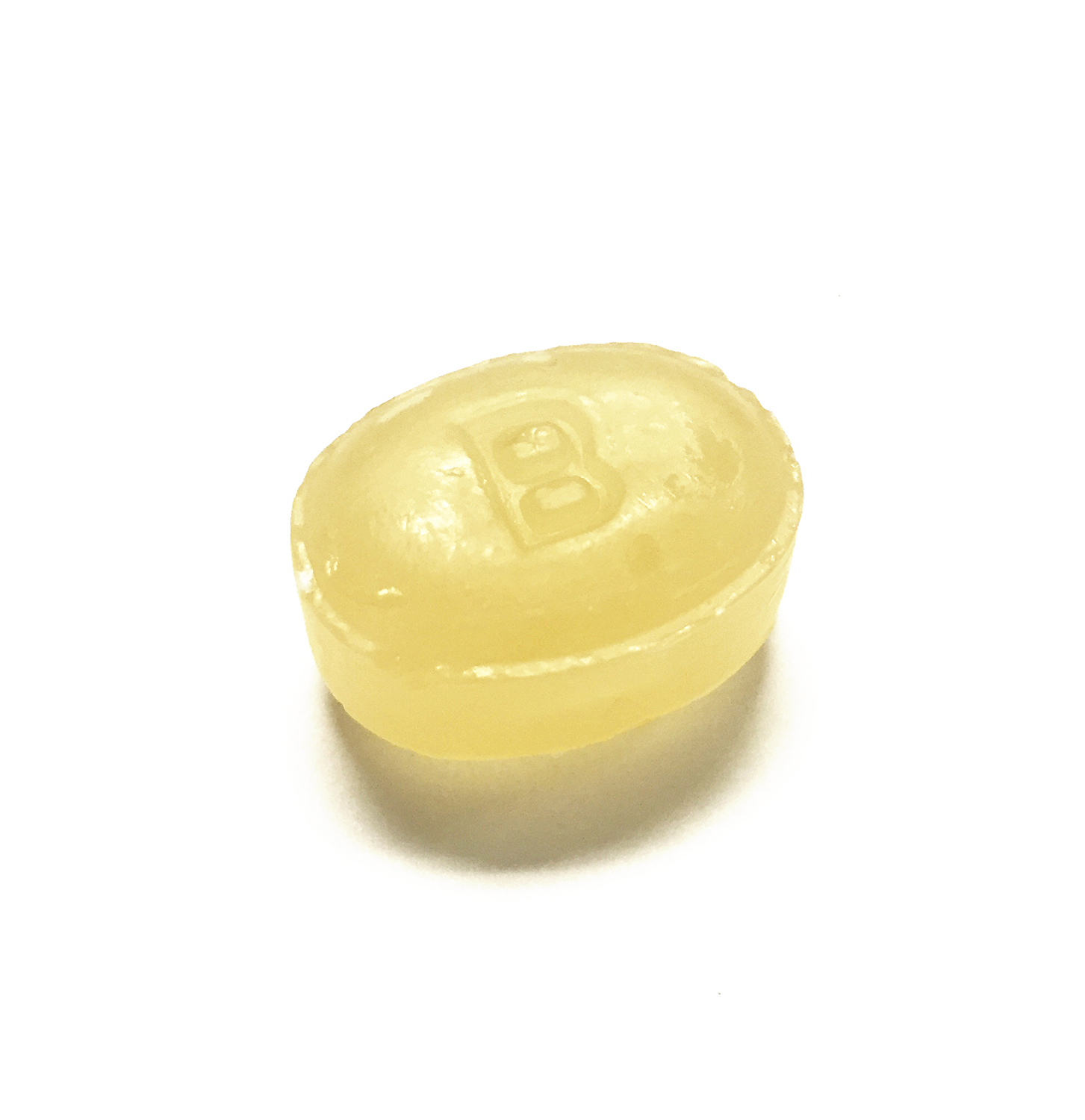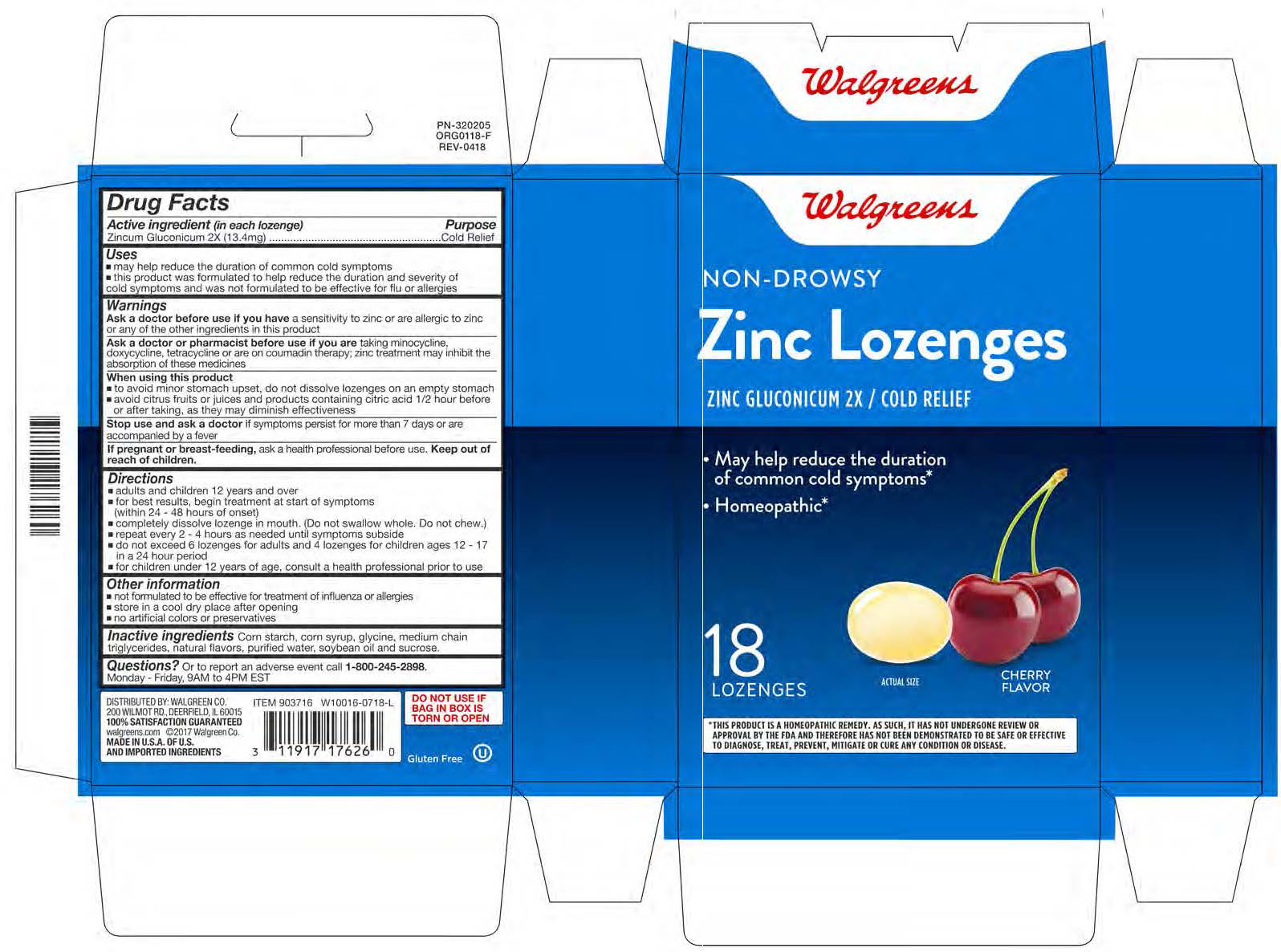 DRUG LABEL: cold relief
NDC: 0363-1090 | Form: LOZENGE
Manufacturer: Walgreen Company
Category: homeopathic | Type: HUMAN OTC DRUG LABEL
Date: 20211228

ACTIVE INGREDIENTS: ZINC GLUCONATE 2 [hp_X]/1 1
INACTIVE INGREDIENTS: SUCROSE

Zincum Gluconicum 2X (13.4mg)

Active ingredient (in each lozenge)

Zincum Gluconicum 2X (13.4 mg)

Purpose

Cold Relief

Uses

- may help reduce the duration of common cold symptoms
- this product was formulated to help reduce the duration and severity of cold symptoms and was not formulated to be effective for flu or allergies

Warnings

Ask a doctor before use if you have a sensitivity to zinc or are allergic to zinc or any of the other ingredients in this product

Ask a doctor or pharmacist before use if you are now taking minocycline, doxycycline, tetracycline or are on coumadin therapy; zinc treatment may inhibit the absorption of these medicines

When using this product

to avaid minor stomach upset, do not dissolve lozenges on an empty stomach

avoid citrus fruits or juices and products containing citric acid 1/2 hour before or after taking, as they may diminish effectiveness

Stop use and ask a doctor if symptoms persist for more than 7 days or are accompanied by a fever

PREGNANCY OR BREAST FEEDING

If pregnant or breast-feeding, ask a health professional before use.

Keep out of reach of children.

Directions

adults and children 12 years and over

for best results, begin treatment at start of symptoms (within 24 - 48 hours of onset)

completely dissolve lozenges in mouth. (Do not swallow whole. Do not chew.)

repeat every 2 - 4 hours as needed until symptoms subside

do not exceed 6 lozenges for adults and 4 lozenges for children ages 12 - 17 in a 24 hour period

for children under 12 years of age, consult a health professional prior to use

Other information

not formulated to be effective for treatment of influenza or allergies

store in a cool dry place after opening

no artificial colors or preservatives

INACTIVE INGREDIENT

Inactive ingredients: Corn starch, corn syrup, glycine, medium chain triglycerides, natural flavors, purified water, soybean oil and sucrose.

QUESTIONS

Questions? Or to report an adverse event call 1-800-245-2898. Monday through Friday, 9AM to 4PM EST